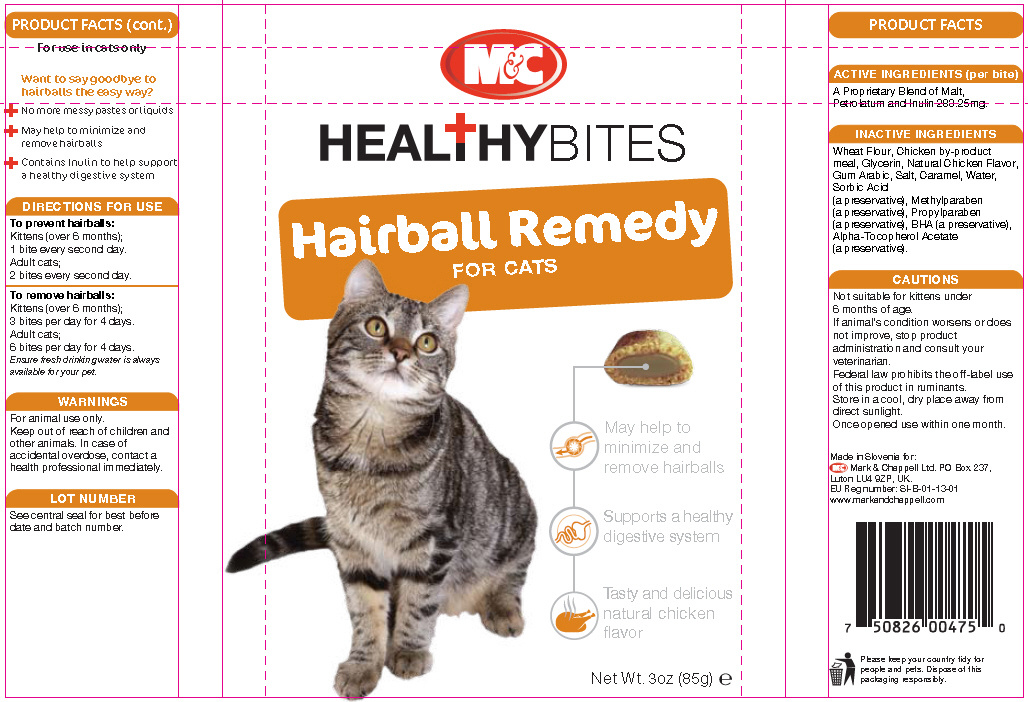 DRUG LABEL: Healthy Bites Hairball Remedy for Cats
								
NDC: 28689-475 | Form: WAFER
Manufacturer: Mark and Chappell Ltd
Category: animal | Type: OTC ANIMAL DRUG LABEL
Date: 20130620

ACTIVE INGREDIENTS: Barley Malt Syrup .1435 g/.65 g; Petrolatum .1365 g/.65 g; Inulin .0032 g/.65 g
INACTIVE INGREDIENTS: Wheat; Chicken; Glycerin; Chicken Liver; Acacia; Sodium Chloride; Caramel; Water; Sorbic Acid; Methylparaben; Propylparaben; Butylated Hydroxyanisole; Alpha-Tocopherol Acetate

ACTIVE INGREDIENTS (per bite)

A proprietary blend of malt, petrolatum and inulin

INACTIVE INGREDIENTS

Wheat Flour, Chicken by-product meal, Glycerin, Natural Chicken Flavor, Gum Arabic, Salt, Caramel, Water, Sorbic Acid (a preservative), Methylparaben (a preservative), Propylparaben (a preservative), BHA (a preservative), Alpha-Tocopherol Acetate (a preservative)

GENERAL PRECAUTIONS

CAUTIONS

Not suitable for kittens under 6 months of age.
If animal's condition worsens or does not improve, stop product administration and consult your veterinarian.
Federal law prohibits the off-label use of this product in ruminants.
Store in a cool, dry place away from direct sunlight.
Once opened use within one month.

For use in cats only.

DESCRIPTION

Want to say goodbye to hairballs the easy way?

- No more messy pastes or liquids
- May help to minimize and remove hairballs
- Contains inulin to help support a healthy digestive system

DIRECTIONS FOR USE

To prevent hairballs:
Kittens (over 6 months): 1 bite every second day
Adult Cats: 2 bites every second day

To remove hairballs:
Kittens (over 6 months): 3 bites per day for 4 days
Adult Cats: 6 bites per day for 4 days

Ensure fresh drinking water is always available for your pet.

WARNINGS

For animal use only.
Keep out of reach of children and other animals. In case of accidental overdose, contact a health care professional immediately.

PACKAGE LABEL

Healthy Bites Hairball Remedy For Cats

Net Wt. 3oz (85g) e